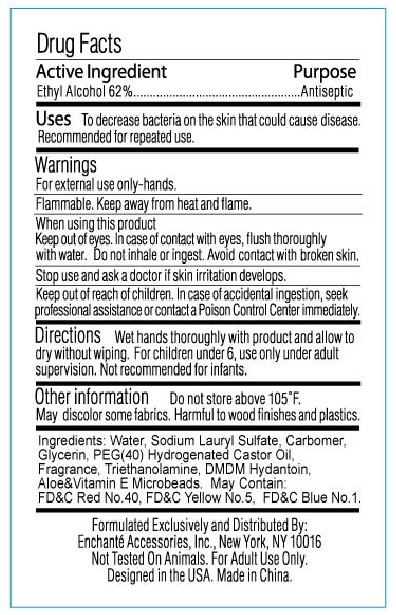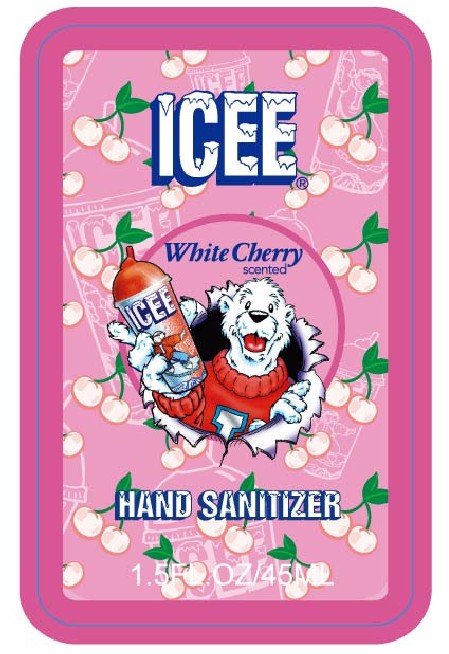 DRUG LABEL: Icee White Cherry Scented Hand Sanitizer
NDC: 34460-6009 | Form: LIQUID
Manufacturer: Zhejiang Blue Dream Cosmetics Co., Ltd.
Category: otc | Type: HUMAN OTC DRUG LABEL
Date: 20101007

ACTIVE INGREDIENTS: ALCOHOL 62 g/100 g
INACTIVE INGREDIENTS: WATER 35.16 g/100 g; GLYCERIN 0.2 g/100 g; TROLAMINE 0.2 g/100 g; CARBOMER HOMOPOLYMER TYPE A 0.2 g/100 g; POLYOXYL 40 HYDROGENATED CASTOR OIL 0.1 g/100 g; DMDM HYDANTOIN 0.02 g/100 g; FD&C YELLOW NO. 5 0.002 g/100 g; FD&C BLUE NO. 1 0.003 g/100 g; FD&C RED NO. 40 0.005 g/100 g; SODIUM LAURYL SULFATE 2 g/100 g; ALPHA-TOCOPHEROL 0.01 g/100 g

DRUG FACT

Active Ingredient Ethyl Alcohol 62%

Purpose Antiseptic

Uses:
To decrease bacteria on skin that could cause disease
Recommended for repeated use

Warnings:
For external use only
Flammable. Keep away from heat and flame.
When using this product
* Keep out of eyes. In case of contact with eyes, flush thoroughly with water
* Avoid contact with broken skin
* Do not inhale or ingest

Stop use and ask a doctor if skin irritation develops

Keep out of reach of children. In case of accidental ingestion, seek professional assistance or contact a Poison Control Center immediately.

Directions:
Wet hands thoroughly with product and allow to dry without wiping
For children under 6, use only under adult supervision.
Not recommended for infants

Other Information
* Do not store above 105F
* May discolor some fabrics
* Harmful to wood finishes and plastics

INACTIVE INGREDIENT

Water, Sodium Lauryl Sulfate, Carbomer, Glycerin, Triethanolamine, Fragrance, PEG-40 Hydrogenated Castor Oil, DMDM Hydantoin, Hydrogenated Jojoba Oil, Aloe and Vitamin E Microbeads. May Contain: FD and C Blue No. 1, FD and C Red No. 40, FD and C Yellow No. 5

PACKAGE LABEL

fron

PACKAGE LABEL

back